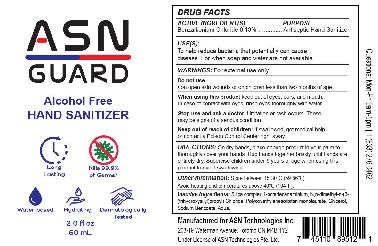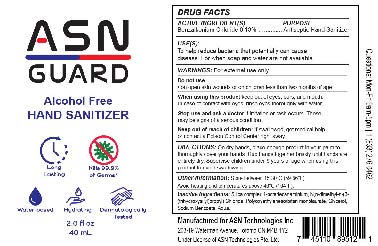 DRUG LABEL: ASN Guard Hand Sanitizer
NDC: 82294-002 | Form: SPRAY
Manufacturer: ASN Technologies Inc
Category: otc | Type: HUMAN OTC DRUG LABEL
Date: 20211214

ACTIVE INGREDIENTS: BENZALKONIUM CHLORIDE 0.078 g/60 mL
INACTIVE INGREDIENTS: GLYCERIN; WATER; SODIUM BENZOATE; POLYSORBATE 20; OCTADECYLDIMETHYL(3-TRIHYDROXYSILYLPROPYL)AMMONIUM CHLORIDE

ASN Guard Hand Sanitizer

Active Ingredient

Benzalkonium Chloride 0.13%

Purpose

Antiseptic

Uses

To help reduce bacteria that potentially can cause disease. For when soap and water are not available.

Warnings

For external use only.

Do Not Use

on open skin wounds or on children less than two months of age

When using this product

keep out of eyes, ears, and mouth. In case of contact with eyes, rinse eyes thoroughly with water.

Stop use and ask a doctor

if irritation or rash occurs. These may be signs of a serious condition.

Keep out of reach of children.

If swallowed, get medical help or contact a Poison Control Center right away.

Directions

On dry hands, place enough product in your palm to thoroughly cover your hands. Rub hands together briskly until hands are entirely dry. Supervise children under 6 years of age when using this product to avoid swallowing.

Other Information

Store between 15-30C (59-86F)
Avoid heating and temperatures above 40C (104F)

Inactive Ingredients

Silica complex 1-octadecanaminium, N,n-dimethyl-n-(3-(trihydroxysilyl)propyl) Chloride, Polyoxyethylenesorbitan monolaurate, Glycerol, Sodium Benzoate, Aqua